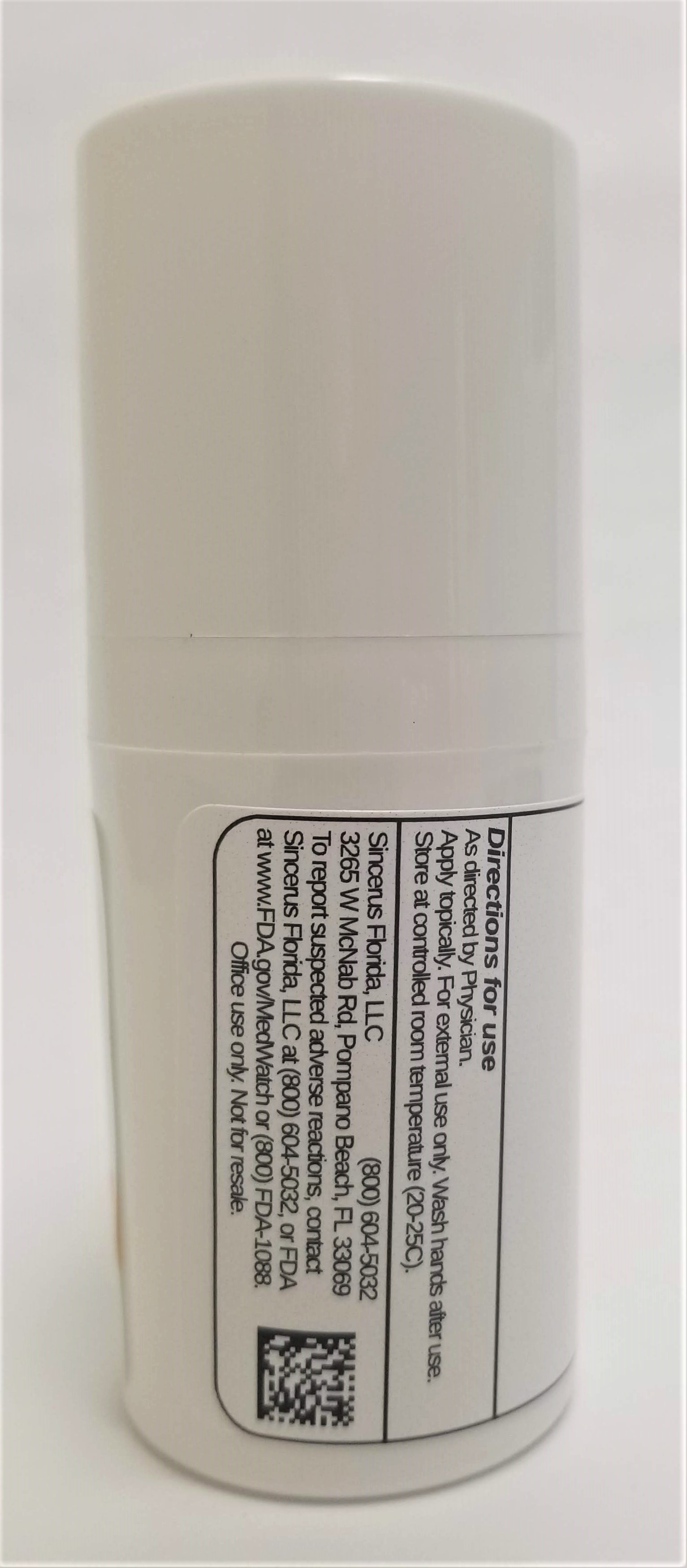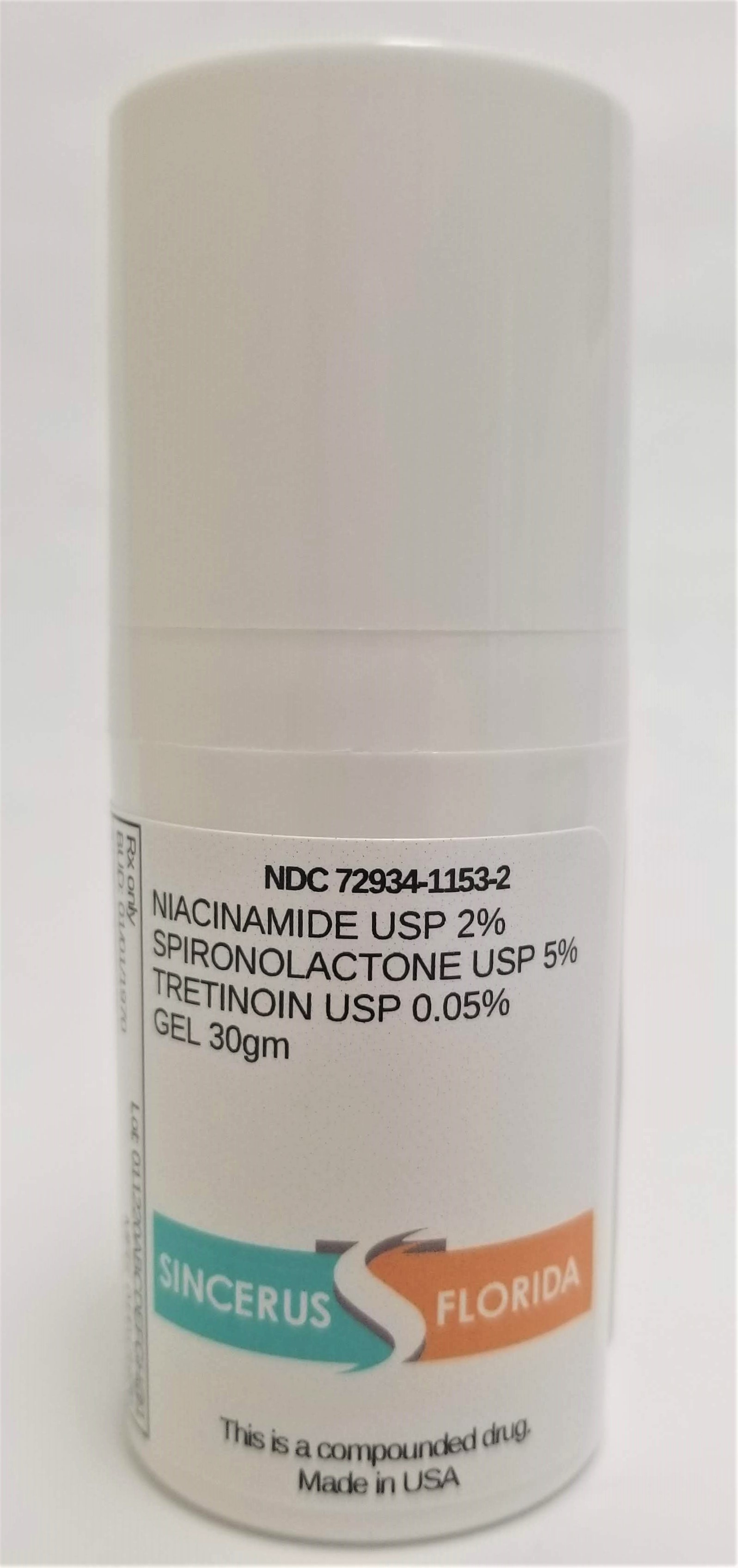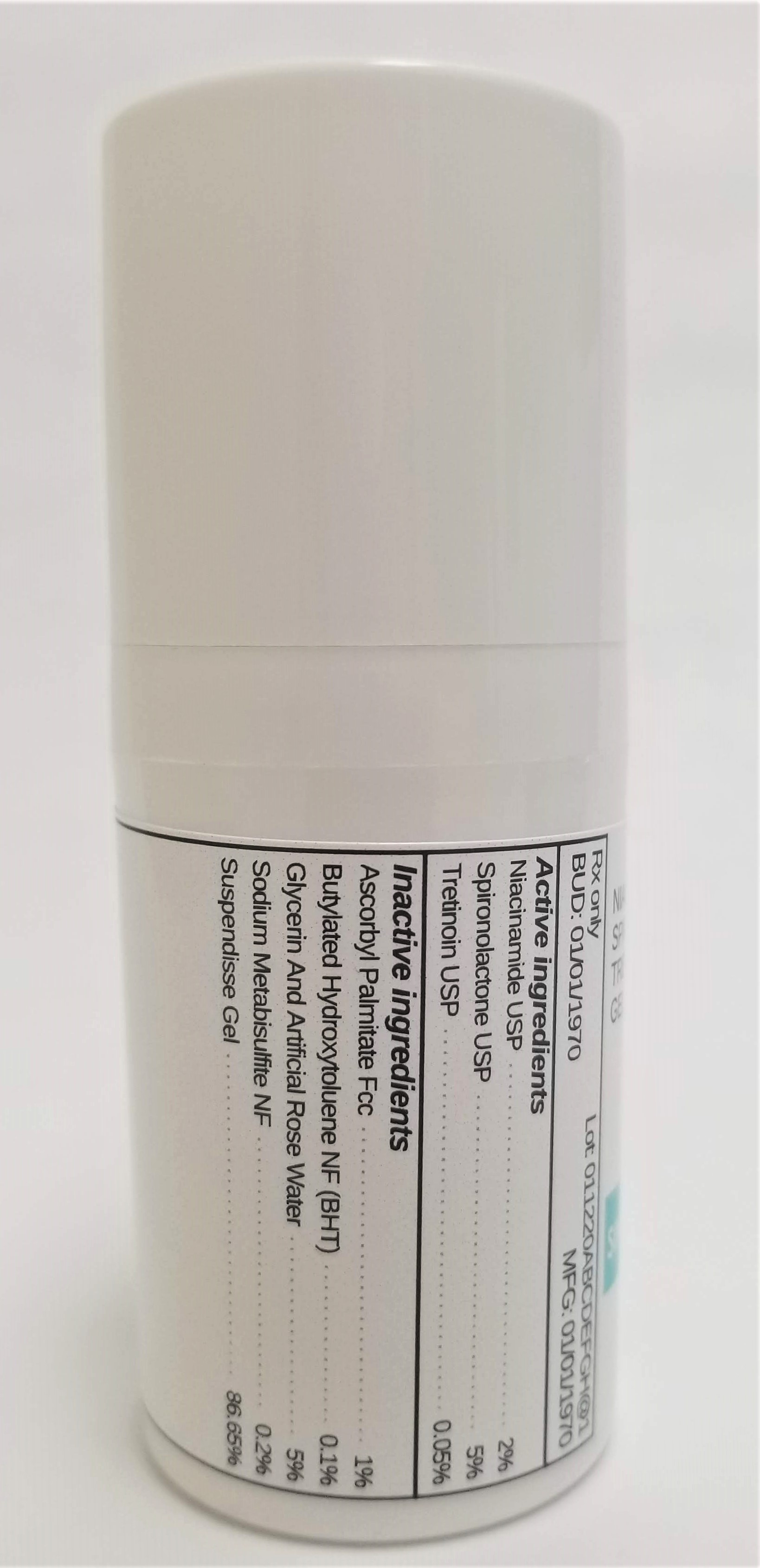 DRUG LABEL: NIACINAMIDE 2% / SPIRONOLACTONE 5% / TRETINOIN 0.05%
NDC: 72934-1153 | Form: GEL
Manufacturer: Sincerus Florida LLC
Category: prescription | Type: HUMAN PRESCRIPTION DRUG LABEL
Date: 20190502

ACTIVE INGREDIENTS: NIACINAMIDE 2 g/100 g; TRETINOIN 0.05 g/100 g; SPIRONOLACTONE 5 g/100 g

NIACINAMIDE 2% / SPIRONOLACTONE 5% / TRETINOIN 0.05%